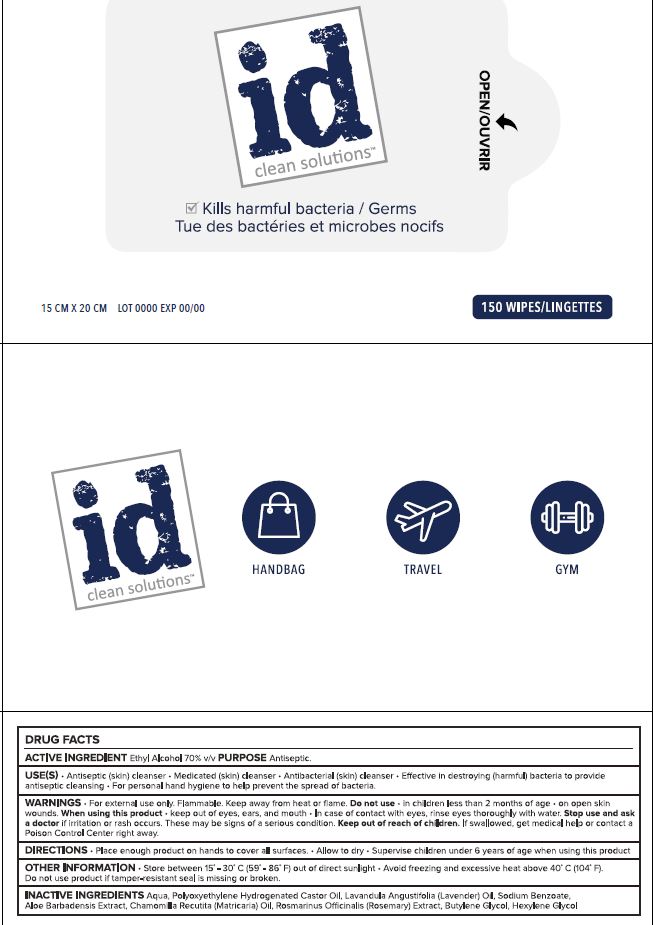 DRUG LABEL: Innovative Display Hand Sanitizing Tissue 150pcs
NDC: 74002-0002 | Form: LIQUID
Manufacturer: DongbangCosmetics Co., ltd.
Category: otc | Type: HUMAN OTC DRUG LABEL
Date: 20200811

ACTIVE INGREDIENTS: ALCOHOL 70 mL/100 g
INACTIVE INGREDIENTS: HEXYLENE GLYCOL; ROSEMARY; SODIUM BENZOATE; CHAMOMILE; WATER; LAVENDER OIL; BUTYLENE GLYCOL; ALOE VERA LEAF; PEG-60 HYDROGENATED CASTOR OIL

ACTIVE INGREDIENT

alcohol

Purpose

Purpose: Antiseptic

Use

 Hand sanitizing to help reduce bacteria on the skin

Warnings

 For external use only.
 Flammable, keep away from fire or flame.
 When using this product, avoid contact with the eyes. In case of contact, rinse eyes thoroughly with water.
 Stop use and ask a doctor if irritation or redness appears and lasts.

 Keep out of reach of children. If swallowed, get medical help or contact a Poison Control Center immediately.

Directions

 Take suitable amount of sanitizer in the hand. Wet thoroughly and rub hands together until dry

INACTIVE INGREDIENT

PEG-60 Hydrogenated Castor Oil
Lavandula Angustifolia (Lavender) Oil
Butylene Glycol
Aloe Barbadensis Extract
Chamomilla Recutita (Matricaria) Oil
Sodium Benzoate
Water
Hexylene Glycol
Rosmarinus Officinalis (Rosemary) Extract